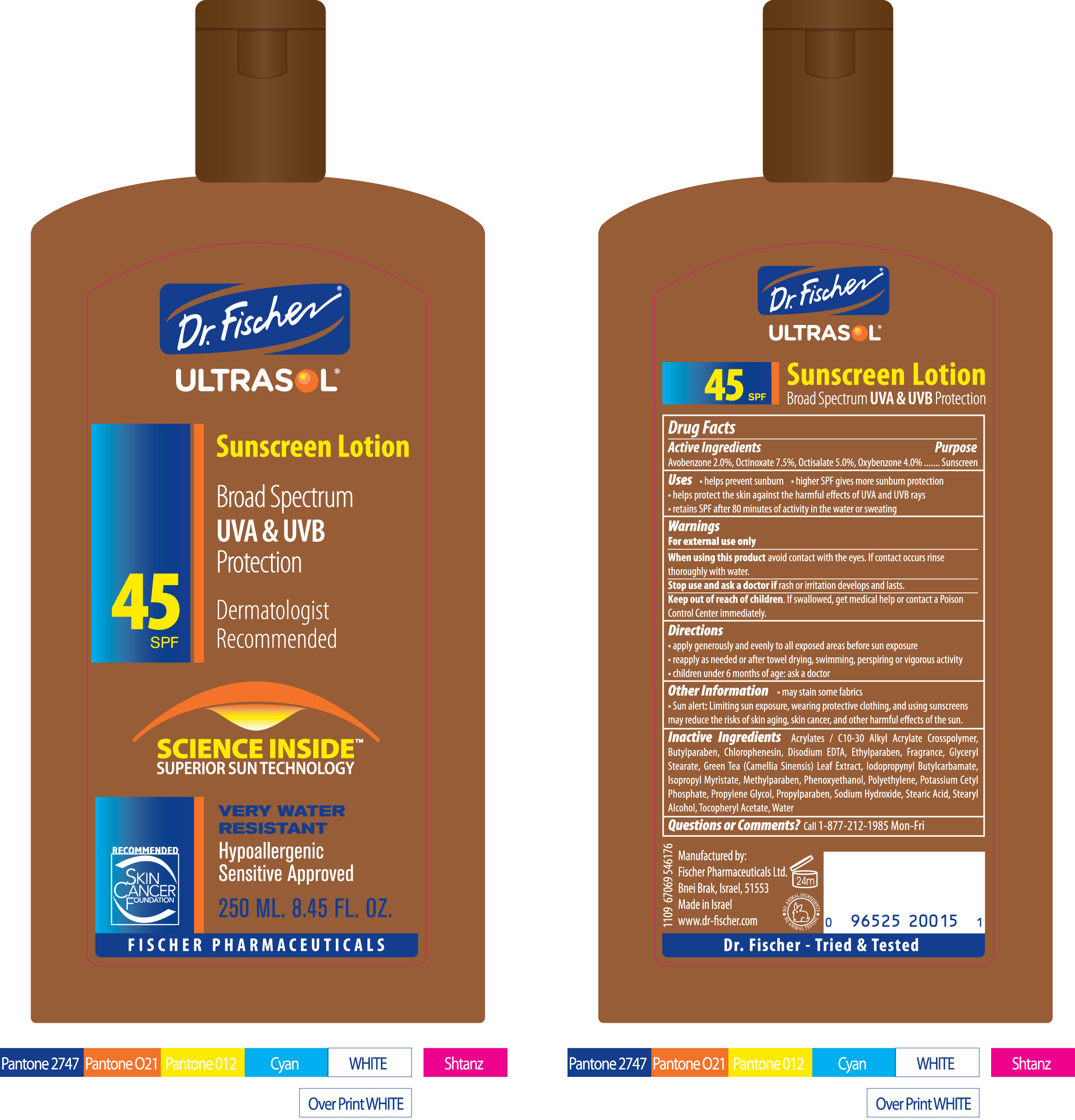 DRUG LABEL: ULTRASOL
NDC: 59886-355 | Form: LOTION
Manufacturer: Fischer Pharmaceuticals Ltd.
Category: otc | Type: HUMAN OTC DRUG LABEL
Date: 20100729

ACTIVE INGREDIENTS: Avobenzone 2 g/100 g; Octinoxate 7.5 g/100 g; Octisalate 5 g/100 g; Oxybenzone 4 g/100 g
INACTIVE INGREDIENTS: Butylparaben; Chlorphenesin; EDETATE DISODIUM; Ethylparaben; GLYCERYL MONOSTEARATE; Isopropyl Myristate; Methylparaben; Phenoxyethanol; Propylene Glycol; Propylparaben; Sodium Hydroxide; Stearic Acid; Stearyl Alcohol; ALPHA-TOCOPHEROL ACETATE; Water

Dr. Fischer ULTRASOL Sunscreen Lotion SPF45 125 ml

Drug Facts

Active Ingredients Purpose
Avobenzone 2.0%, Octinoxate 7.5%, Octisalate 5.0%, Oxybenzone 4.0% ....... Sunscreen

Uses

• helps prevent sunburn • higher SPF gives more sunburn protection
• helps protect the skin against the harmful effects of UVA and UVB rays
• retains SPF after 80 minutes of activity in the water or sweating

Warnings

For external use only

When using this product

avoid contact with the eyes. If contact occurs rinse
thoroughly with water.

Stop use and ask a doctor if

if rash or irritation develops and lasts.

Keep out of reach of children

If swallowed, get medical help or contact a Poison
Control Center immediately.

Directions

• apply generously and evenly to all exposed areas before sun exposure
• reapply as needed or after towel drying, swimming, perspiring or vigorous activity
• children under 6 months of age: ask a doctor

Other Information

• may stain some fabrics
• Sun alert: Limiting sun exposure, wearing protective clothing, and using sunscreens
may reduce the risks of skin aging, skin cancer, and other harmful effects of the sun.

Inactive Ingredients

Acrylates / C10-30 Alkyl Acrylate Crosspolymer,
Butylparaben, Chlorophenesin, Disodium EDTA, Ethylparaben, Fragrance, Glyceryl
Stearate, Green Tea (Camellia Sinensis) Leaf Extract, Iodopropynyl Butylcarbamate,
Isopropyl Myristate, Methylparaben, Phenoxyethanol, Polyethylene, Potassium Cetyl
Phosphate, Propylene Glycol, Propylparaben, Sodium Hydroxide, Stearic Acid, Stearyl
Alcohol, Tocopheryl Acetate, Water.

Questions or Comments?

Call 1-877-212-1985 Mon-Fri

PACKAGE LABEL

Section Text
Dr. Fischer ULTRASOL
Sunscreen Lotion SPF 45
Broad Spectrum
UVA and UVB Protection
Dermatologist Recommended
Science InsideTM Superior Sun Technology
Very Water Resistant
Hypoallergenic
Sensitive Approved
Recommended - Skin Cancer Foundation
125 ML. 4.22 FL. OZ.
FISCHER PHARMACEUTICALS
(Back of Package):
Manufactured by:
Fischer Pharmaceuticals Ltd.
Bnei Brak, Israel, 51553
Made in Israel
www.dr-fischer.com
NO ANIMAL INGREDIENTS - NO ANIMAL TESTING
24m
Dr. Fischer Tried and Tested